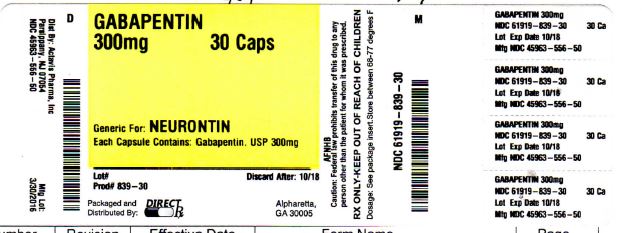 DRUG LABEL: GABAPENTIN
NDC: 61919-839 | Form: CAPSULE
Manufacturer: DIRECT RX
Category: prescription | Type: HUMAN PRESCRIPTION DRUG LABEL
Date: 20160404

ACTIVE INGREDIENTS: GABAPENTIN 300 mg/1 1
INACTIVE INGREDIENTS: FERROSOFERRIC OXIDE; SHELLAC; STARCH, CORN; D&C YELLOW NO. 10; FD&C BLUE NO. 1; FD&C BLUE NO. 2; FD&C RED NO. 40; GELATIN; MANNITOL; SODIUM LAURYL SULFATE; TALC; FERRIC OXIDE YELLOW; PROPYLENE GLYCOL; FERRIC OXIDE RED; SILICON DIOXIDE; TITANIUM DIOXIDE

GABAPENTIN 300mg 30CAPS